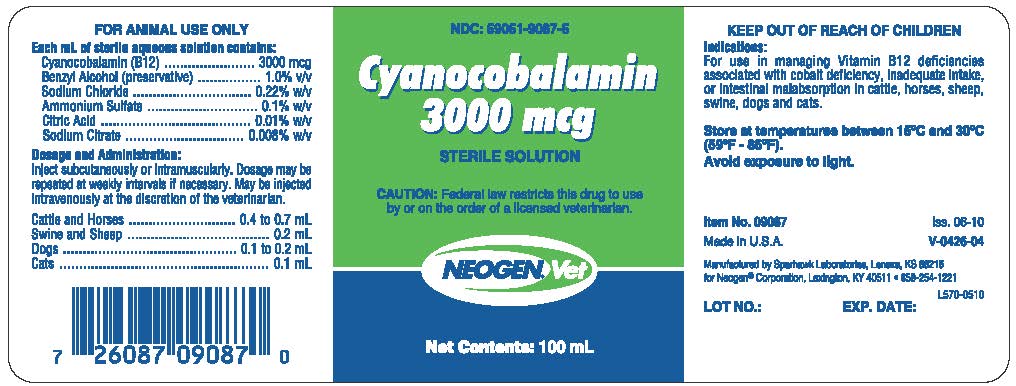 DRUG LABEL: Cyanocobalamin 3000 mcg
NDC: 59051-9087 | Form: INJECTION
Manufacturer: Neogen Corporation - Nandino
Category: animal | Type: PRESCRIPTION ANIMAL DRUG LABEL
Date: 20231218

ACTIVE INGREDIENTS: CYANOCOBALAMIN 3000 ug/1 mL

Cyanocobalamin 3000 mcg

INDICATIONS AND USAGE

FOR ANIMAL USE ONLY

KEEP OUT OF REACH OF CHILDREN

CAUTION: Federal law restricts this drug to use by or on the order of a licensed veterinarian.

Indications:

For use in managing Vitamin B12 deficiencies associated with cobalt deficiency, inadequate intake, or intestinal malabsorption in cattle, horses, sheep, swine, dogs and cats.

DOSAGE AND ADMINISTRATION

Inject subcutaneously or intramuscularly. Dosage may be repeated at wekly intervals if necessary. May be injected intravenously at the discretion of the veterinarian.

Cattle and Horses..........................0.4 to 0.7 mL

Swine and Sheep....................................0.2 mL

Dogs............................................0.1 to 0.2 mL

Cats......................................................0.1 mL

COMPOSITION

Each mL of sterile aqueous solution contains:
Cyanocobalamin (B12)...................... 3000 mcg

Banzyl Alchohol (preservative)............ 1.0% v/v

Sodium Citrate ..............................0.008% w/v

Ammonium Sulfate........................... 0.1% w/v

Citric Acid...................................... 0.01% w/v

Sodium Citrate............................. 0.008% w/v

STORAGE AND HANDLING

Store at temperatures between 15o to 30oC (59o - 86oF).

Avoid exposure to light.